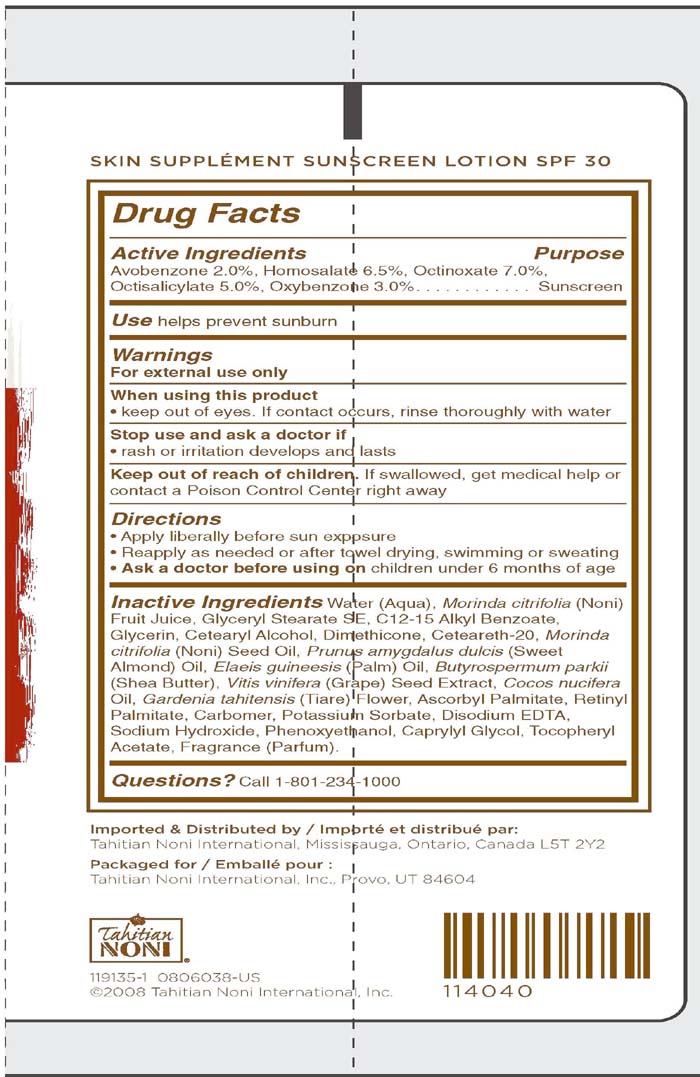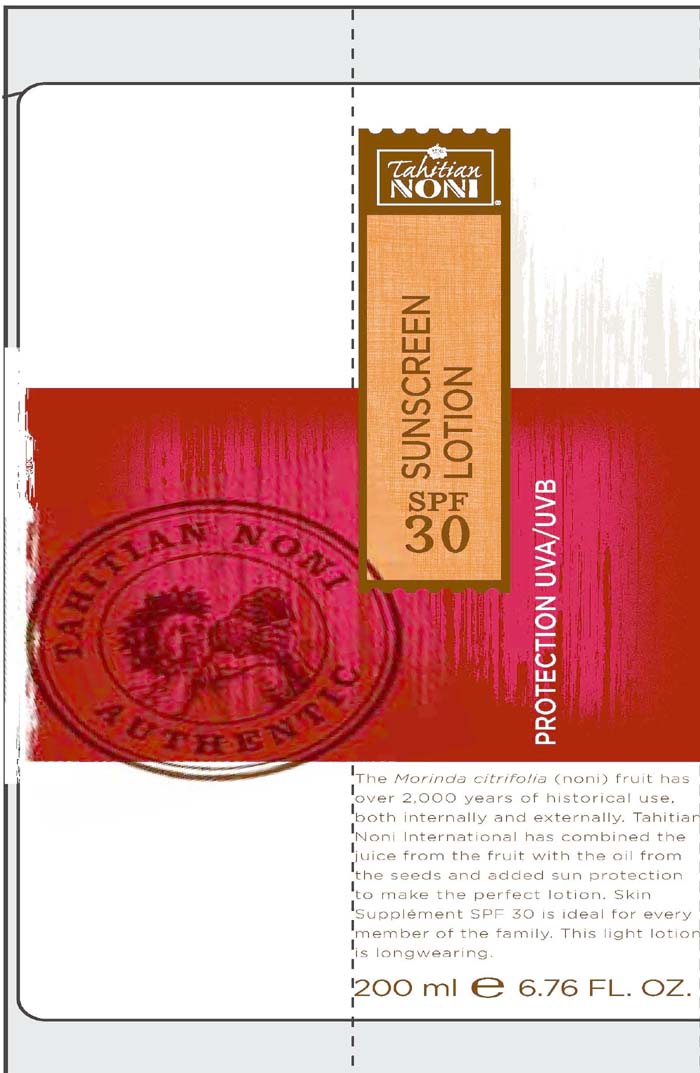 DRUG LABEL: Tahitian Noni
NDC: 14743-536 | Form: LOTION
Manufacturer: Tahitian Noni International
Category: otc | Type: HUMAN OTC DRUG LABEL
Date: 20120130

ACTIVE INGREDIENTS: AVOBENZONE 2.0 mL/100 mL; HOMOSALATE 6.5 mL/100 mL; OCTINOXATE 7.0 mL/100 mL; OCTISALATE 5.0 mL/100 mL; OXYBENZONE 3.0 mL/100 mL
INACTIVE INGREDIENTS: MORINDA CITRIFOLIA FRUIT; GLYCERYL MONOSTEARATE; ALKYL (C12-15) BENZOATE; GLYCERIN; CETOSTEARYL ALCOHOL; DIMETHICONE; MORINDA CITRIFOLIA SEED OIL; VITIS VINIFERA SEED; SHEA BUTTER; COCONUT OIL; GARDENIA TAITENSIS FLOWER; ASCORBYL PALMITATE; VITAMIN A PALMITATE; POTASSIUM SORBATE; EDETATE DISODIUM; SODIUM HYDROXIDE; PHENOXYETHANOL; CAPRYLYL GLYCOL

Sunscreen Lotion SPF 30

Active Ingredients purpose

Avobenzone 2% Sunscreen

Homosalate 6.5% Sunscreen

Octinoxate 7% Sunscreen

Octisalate 5% Sunscreen

Oxybenzone 3% Sunscreen

PURPOSE

Use helps prevent sunburn

Keep out of reach of children

Stop use and ask a doctor if

-rash or irritation develops and lasts

Warnings
For External Use only
When using this product
Keep out of eyes. If contact occurs, rinse thoroughly with water
.
If swallowed, get medical help or contact a poison control center right away.

Directions:
Apply liberally before sun exposure
Reapply as needed or after towel drying, swimming, or sweating
Ask a doctor before using on children under 6 months of age

INACTIVE INGREDIENT

Inactive Ingredients: Water (Aqua), Morinda citrifolia (Noni) fruit juice, Glyceryl Stearate SE, C12-15 Alkyl Benzoate, Glycerin, Cetearyl Alcohol, Dimethicone, Ceteareth-20, Morinda citrifolia (Noni) Seed Oil, Prunus Amygdalus dulcis (sweet almond) Oil, Elaeis guinesssis (palm) Oil, Butyrospermum parkii (Shea Butter), Vitis vinifera (grape) seed extract, cocos nucifera oil, Gardenia tahitensis (Tiare) flower, Ascorbyl palmitate, retinyl palmitate Carbomer,potassium sorbate, disodium EDTA, Sodium Hydroxide, phenoxy ethanol, caprylyl glycol, tocopheryl acetate, Fragrance (parfum).

PACKAGE LABEL

Tahitian Noni

Sunscreen Lotion
SPF 30

200 ml 6.76 fl.oz.